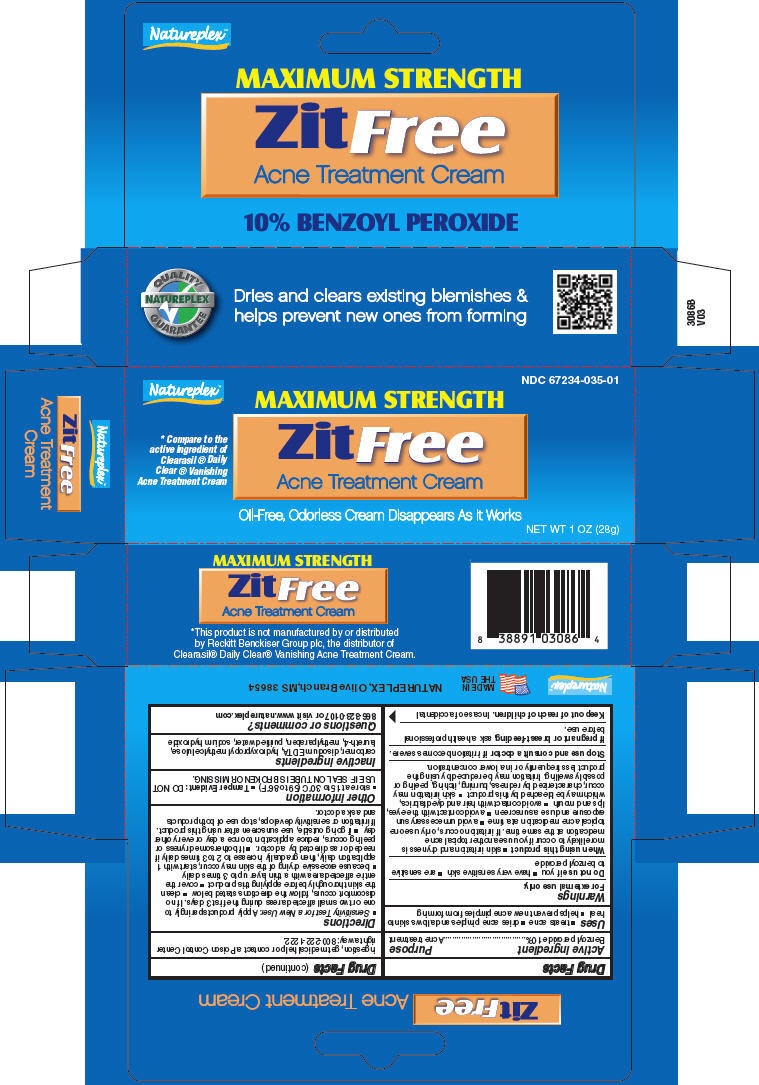 DRUG LABEL: ZITFREE
NDC: 67234-035 | Form: OINTMENT
Manufacturer: Natureplex, LLC
Category: otc | Type: HUMAN OTC DRUG LABEL
Date: 20260129

ACTIVE INGREDIENTS: BENZOYL PEROXIDE 100 mg/1 g
INACTIVE INGREDIENTS: CARBOMER HOMOPOLYMER TYPE C (ALLYL PENTAERYTHRITOL CROSSLINKED); EDETATE DISODIUM; HYPROMELLOSE, UNSPECIFIED; LAURETH-4; METHYLPARABEN; WATER; SODIUM HYDROXIDE

ZITFREE
ACNE TREATMENT

Drug Facts

Active ingredient

Benzoyl peroxide 10%

Purpose

Acne treatment

Uses

- treats acne
- dries acne pimples and allows skin to heal
- helps prevent new acne pimples from forming

Warnings

For external use only.

Do not use if you

- have very sensitive skin
- are sensitive to benzoyl peroxide

When using this product

- skin irritation and dryness is more likely to occur if you use another topical acne medication at the same time. If irritation occurs, only use one topical acne medication at a time
- avoid unnecessary sun exposure and use a sunscreen
- avoid contact with the eyes, lips and mouth
- avoid contact with hair and dyed fabrics, which may be bleached by this product
- skin irritation may occur, characterized by redness, burning, itching, peeling or possibly swelling. Irritation may be reduced by using the product less frequently or in a lower concentration.

Stop use and consult a doctor if irritation becomes severe.

PREGNANCY OR BREAST FEEDING

If pregnant or breast-feeding, ask a health professional before use.

Keep out of reach of children. In case of accidental ingestion, get medical help or contact a Poison Control Center right away: 800-222-1222.

Directions

- Sensitivity Test for a New User. Apply product sparingly to one or two small affected areas during the first 3 days. If no discomfort occurs, follow the directions stated below
- clean the skin thoroughly before applying this product
- cover the entire affected area with a thin layer up to 3 times daily
- because excessive drying of the skin may occur, start with 1 application daily, then gradually increase to 2 to 3 times daily if needed or as directed by a doctor.
- If bothersome dryness or peeling occurs, reduce application to once a day or every other day
- if going outside, use sunscreen after using this product. If irritation or sensitivity develops, stop use of both products and ask a doctor.

Other information

- store at 15 to 30°C (59 to 86°F)
- Tamper Evident: DO NOT USE IF SEAL ON TUBE IS BROKEN OR MISSING.

Inactive ingredients

carbomer, disodium EDTA, hydroxypropyl methylcellulose, laureth-4, methylparaben, purified water, sodium hydroxide

Questions or comments?

866-323-0107 or visit www.natureplex.com

PRINCIPAL DISPLAY PANEL - 28 g Tube Carton

NDC 67234-035-01

Natureplex™

MAXIMUM STRENGTH

ZitFree
Acne Treatment Cream

* Compare to the
active ingredient of
Clearasil ® Daily
Clear ® Vanishing
Acne Treatment Cream

Oil-Free, Odorless Cream Disappears As It Works

NET WT 1 OZ (28g)